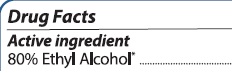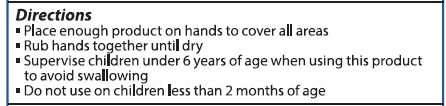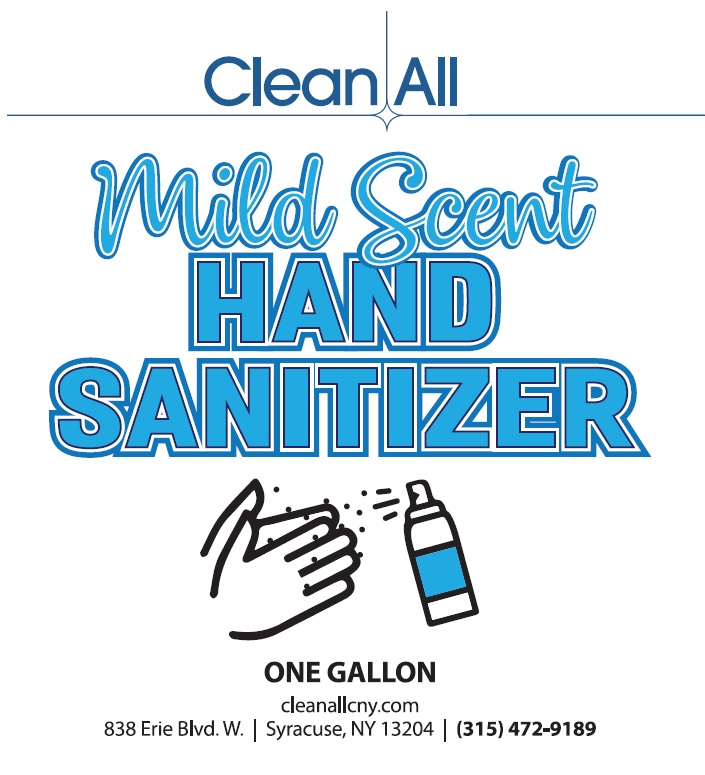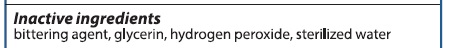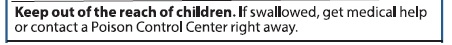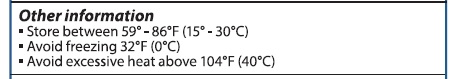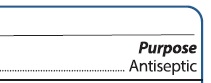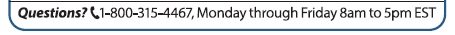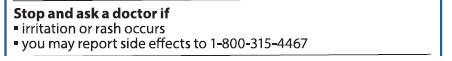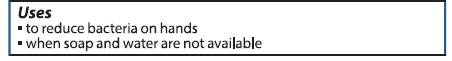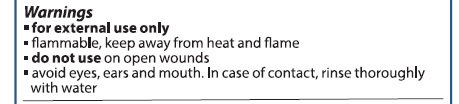 DRUG LABEL: Hand Sanitizer
NDC: 75660-001 | Form: LIQUID
Manufacturer: Solvents and Petroleum Service, Inc.
Category: otc | Type: HUMAN OTC DRUG LABEL
Date: 20200922

ACTIVE INGREDIENTS: ALCOHOL 3028 mL/100 1
INACTIVE INGREDIENTS: GLYCERIN 75 mL/100 1; HYDROGEN PEROXIDE 1 mL/100 1; WATER 681.1 mL/100 1; DENATONIUM BENZOATE 0.4 mL/100 1

Hand Sanitizer

Active ingredients

Active ingredient

80% Ethyl Alcohol

Purpose

Purpose Antiseptic

Uses

to reduce bacteiaon hands. when soap and water are not available

Warnings

- for external use only
- flammable, keep away from heat and flame
- do not use on open wounds
- avoid eyes, ears and mouth. In case of contact, rinse thoroughly with water

STop and ask a doctor if

irritation or rash occurs. you may report side effects to 1-800-315-4467

Keep Out of the Reach of Children

Directions

Place enough product on hands to cover all surfaces. Rub hands together until dry.

Supervise children under 6 years of age when using this product to avoid swallowing.

Do not use on children less than 2 months of age.

Other information

Store between 59-86F (15-30C)

Avoid freezing 32 F

avoid excessive heat above 104F (40C)

Inactive ingredients

nacive ingredients

glycerin, hydrogen peroxide, bittering agent, sterilized water

Directions

Place enough product on hands to cover all surfaces. Rub hands together until dry.

Supervise children under 6 years of age when using this product to avoid swallowing.

Do not use on children less than 2 months of age.

Questions?

Package Label - Principal Display Panel